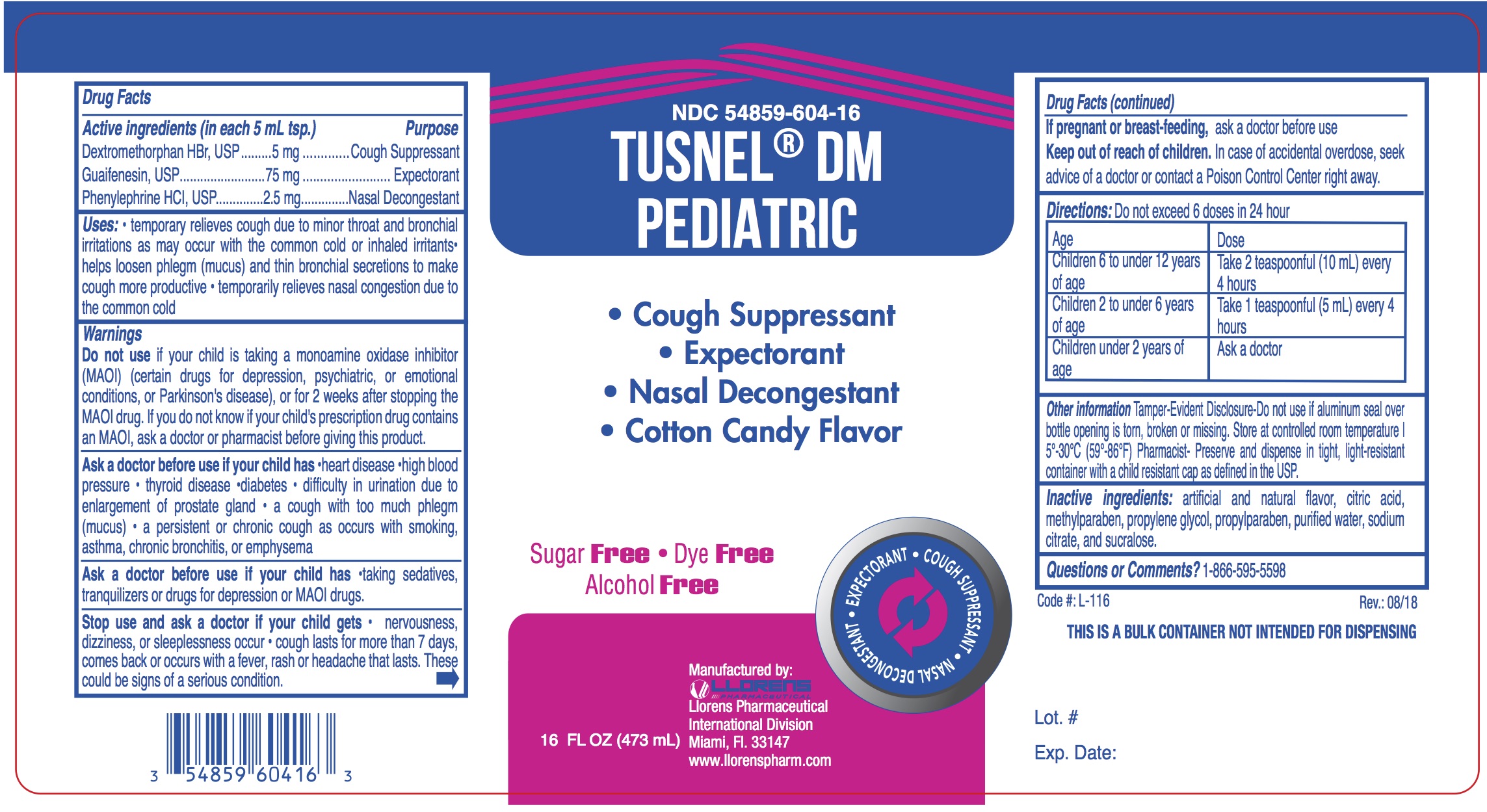 DRUG LABEL: Tusnel Pediatric
NDC: 54859-604 | Form: LIQUID
Manufacturer: Llorens Pharmaceutical International Division, Inc.
Category: otc | Type: HUMAN OTC DRUG LABEL
Date: 20251231

ACTIVE INGREDIENTS: DEXTROMETHORPHAN HYDROBROMIDE 5 mg/5 mL; GUAIFENESIN 75 mg/5 mL; PHENYLEPHRINE HYDROCHLORIDE 2.5 mg/5 mL
INACTIVE INGREDIENTS: ANHYDROUS CITRIC ACID; METHYLPARABEN; PROPYLENE GLYCOL; PROPYLPARABEN; WATER; TRISODIUM CITRATE DIHYDRATE; SUCRALOSE

Llorens-Tusnel DM Ped 604

ACTIVE INGREDIENT

In each 5 mL

Dextromethorphan HBr - 5 mg

Guaifenesin - 75 mg

Phenylephrine HCl - 2.5 mg

Purpose

Cough Suppressant

Expectorant

Nasal Decongestant

Uses

- temporary relieves cough due to minor throat and bronchial irritations as may occur with the common cold or inhaled irritants
- helps loosen phlegm (mucus) and thin bronchial secretions to make cough more productive • temporarily relieves nasal congestion due to the common cold

Warnings

Do not use if your child is taking a monoamine oxidase inhibitor (MAOI) (certain drugs for depression, psychiatric, or emotional conditions, or Parkinson's disease), or for 2 weeks after stopping the MAOI drug. If you do not know if your child's prescription drug contains an MAOI, ask a doctor or pharmacist before giving this product.

Ask a doctor before use if your child has

- heart disease
- high blood pressure
- thyroid disease
- diabetes
- difficulty in urination due to enlargment of prostate gland
- a cough with too much phlegm (mucus)
- a persistent or chronic cough as occurs with smoking, asthma, chronic bronchitis, or emphysema

Ask a doctor before use if your child is

- taking sedatives, tranquilizers or drugs for depression or MAOI drugs.

Stop use and ask a doctor if your child gets

- nervousness, dizziness, or sleeplessness occur
- cough lasts for more than 7 days, comes back or occurs with a fever, rash or headache that lasts. These could be signs of a serious condition.

PREGNANCY OR BREAST FEEDING

If pregnant or breast-feeding, ask a doctor before use

Keep out of reach of children.In case of accidental overdose, seek advice of a doctor or contact a Poison Control Center right away.

DOSAGE AND ADMINISTRATION

Directions: Do not exceed 6 doses in 24 hour

Age | Dose
Children 6 to under 12 years of age | Take 2 teaspoonful (10 mL) every 4 hours
Children 2 to under 6 years of age | Take 1 teaspoonful (5 mL) every 4 hours
Children under 2 years of age | Ask a doctor

INACTIVE INGREDIENT

Inactive ingredients:artificial and natural flavor, citric acid, methylparaben, propylene glycol, propylparaben, purified water, sodium citrate, and sucralose.

Questions or Comments?1-866-595-5598